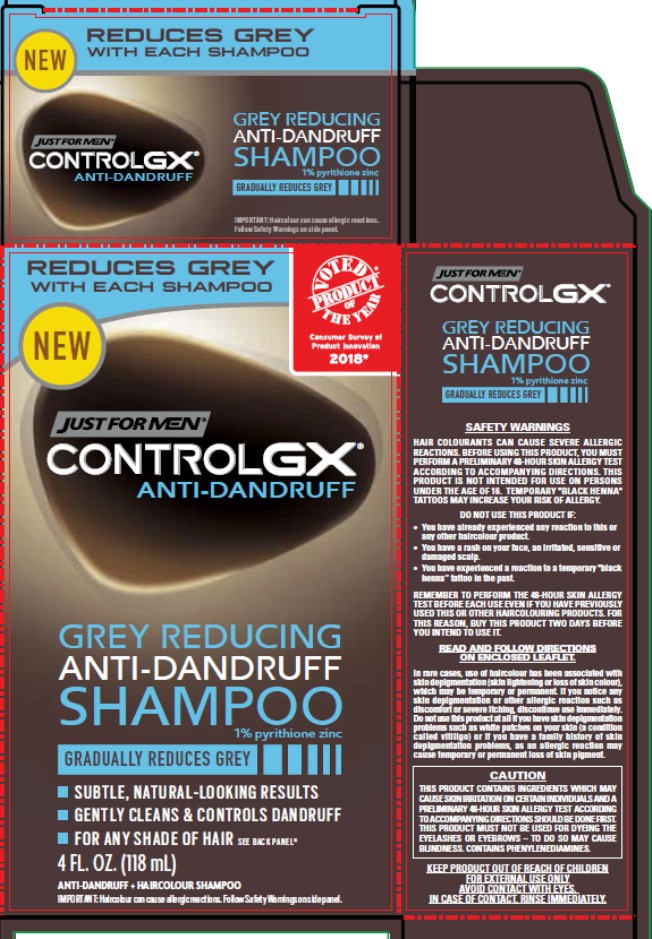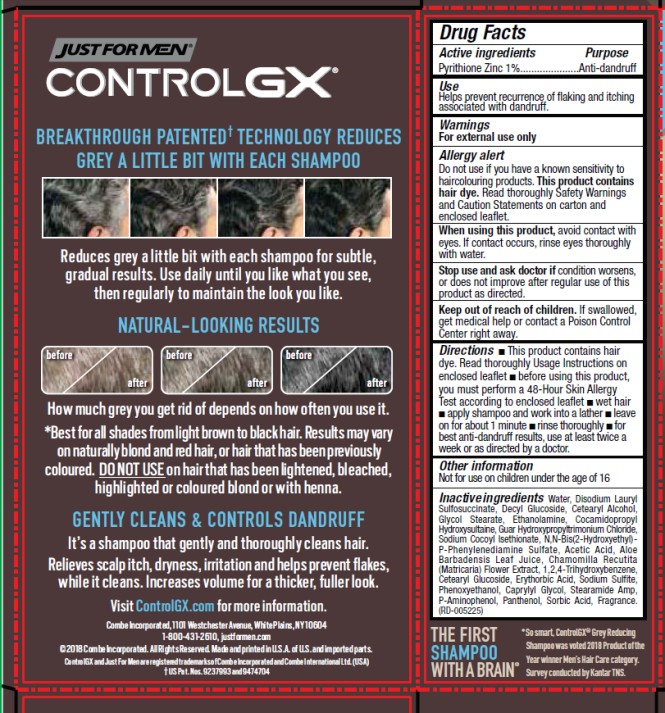 DRUG LABEL: Just For Men Control GX Anti-Dandruff
NDC: 11509-5225 | Form: SHAMPOO
Manufacturer: Combe Incorporated
Category: otc | Type: HUMAN OTC DRUG LABEL
Date: 20241212

ACTIVE INGREDIENTS: PYRITHIONE ZINC 10 mg/1 mL
INACTIVE INGREDIENTS: WATER; DISODIUM LAURYL SULFOSUCCINATE; Decyl Glucoside; CETOSTEARYL ALCOHOL; GLYCOL STEARATE; 2-AMINOETHANOL; COCAMIDOPROPYL HYDROXYSULTAINE; GUAR HYDROXYPROPYLTRIMONIUM CHLORIDE (1.7 SUBSTITUENTS PER SACCHARIDE); SODIUM COCOYL ISETHIONATE; N,N-BIS(2-HYDROXYETHYL)-P-PHENYLENEDIAMINE SULFATE; ACETIC ACID; ALOE VERA LEAF; 1,2,4-TRIHYDROXYBENZENE; CETEARYL GLUCOSIDE; ERYTHORBIC ACID; SODIUM SULFITE; PHENOXYETHANOL; CAPRYLYL GLYCOL; STEARAMIDE AMP; P-AMINOPHENOL; PANTHENOL; SORBIC ACID

Just For Men Control GX Anti-Dandruff Shampoo

JUST FOR MEN® Control GX® Anti-Dandruff Shampoo

Drug Facts

Active ingredient

Pyrithione Zinc 1%

Purpose

Anti-Dandruff

Use

Helps prevent recurrence of flaking and itching associated with dandruff.

Warnings

For external use only

Allergy Alert

Do not use if you have known sensitivity to haircolouring products. This product contains hair dye. Read thoroughly Safety Warnings and Caution Statements on carton and enclosed leaflet.

When using this product

avoid contact with eyes. If contact occurs, rinse eyes thoroughly with water.

Stop use and ask doctor if

condition worsens, or does not improve after regular use of this product as directed.

Keep out of reach of children.

If swallowed, get medical help or contact a Poison Control Center right away.

Directions

- This product contains hair dye. Read thoroughly Usage Instructions on enclosed leaflet
- Before using this product, you must perform a 48-Hour Skin Allergy Test according to enclosed leaflet
- Wet hair
- Apply shampoo and work into a lather
- Leave on for about 1 minute
- Rinse thoroughly
- For best anti-dandruff results, use at least twice a week or as directed by a doctor.

Other Information

Not for use on children under the age of 16

Inactive ingredients

Water, Disodium Lauryl Sulfosuccinate, Decyl Glucoside, Cetearyl Alcohol, Glycol Stearate, Ethanolamine, Cocamidopropyl Hydroxysultaine, Guar Hydroxypropyltrimonium Chloride, Sodium Cocoyl Isethionate, N,N-Bis(2-Hydroxyethyl)-P-Phenylenediamine Sulfate, Acetic Acid, Aloe Barbadensis Leaf Juice, Chamomilla Recutita (Matricaria) Flower Extract, 1,2,4-Trihydroxybenzene, Cetearyl Glucoside, Erythorbic Acid, Sodium Sulfite, Phenoxyethanol, Caprylyl Glycol, Stearamide Amp, P-Aminophenol, Panthenol, Sorbic Acid, Fragrance.

PACKAGE INSERT

48-HOUR SKIN ALLERGY TEST

YOU MUST PERFORM THIS SKIN ALLERGY TEST 48-HOURS BEFORE FIRST USE, AND WHENEVER YOU HAVE NOT USED THIS PRODUCT FOR 2 CONSECUTIVE WEEKS OR MORE, EVEN IF YOU HAVE ALREADY USED THIS OR ANOTHER HAIRCOLOUR PRODUCT WITHOUT ANY ADVERSE REACTION.

Allergic reactions (such as itching, burning, redness, swelling, skin abrasions, eruptions or irritation) to permanent haircolour, including this product, can occur and in rare instances be severe. If you have ever experienced any of these symptoms while using this product, stop using haircolouring products until you consult a doctor, as these are signs that you may have developed an allergy.

- You MUST do this test 48 hours before first use and whenever you have not used this product for 2 consecutive weeks or more. This test is not a guarantee of avoiding future allergic reactions.
- For some users, frequent use of haircolouring products can increase the risk of allergic reactions.
- This test represents an important precaution. However, be aware that even if a test has been carried out, you may still experience an allergic reaction when you use this product.

1) WASH TEST AREA. With mild soap and water, wash an area about the size of a coin on the inside bend of your elbow. Pat dry.

2) APPLY PRODUCT. Peel off freshness tab under cap. Do not use if missing or broken. Squeeze a small amount of product from the tube and spread it thinly with a cotton swab or tissue onto the test area. Place cap back on tube immediately and tightly so it doesn’t lose effectiveness.

3) DO NOT WASH OR COVER TEST AREA FOR 48 HOURS. Examine the test area during this time. If at ANY TIME during the testing, you experience itching, burning, redness, swelling, eruptions, or any irritation, you may be allergic. STOP! Wash area immediately and keep it uncovered. YOU MUST NOT USE this product or ANY OTHER haircolouring product.

If you have NO reaction after 48 hours, you may use the product.

WHAT TO DO IF YOU HAVE A REACTION AT ANY TIME WHILE OR AFTER USING THIS PRODUCT:

- If you experience ANY itching, burning, redness, swelling, eruptions, or irritation, rinse immediately and thoroughly as this may be an indication of an allergic reaction. DO NOT USE this product again. If symptoms persist seek medical attention.
- SEEK MEDICAL ATTENTION if you experience a rapidly spreading rash, dizziness, faintness, difficulty breathing and shortness of breath, tightness of chest, hives, swelling of eyes/face, blistering of skin or scalp weeping.

SAFETY WARNINGS

- If you have ever experienced any allergic reaction (such as itching, burning, redness, swelling, skin abrasions, eruptions or irritation) following use of a haircolouring product, do not use this or any other haircolouring product.
- Always do the 48-Hour Skin Allergy Test before first use, and whenever you have not used this product for 2 consecutive weeks or more.
- Wait at least 24 hours after you have relaxed or straightened your hair before you use this product. Wait 2 weeks after you have used a permanent wave.
- Temporary black henna tattoos may increase your risk of allergy.
- Before use, carefully check the skin area(s) where this product is to be applied for irritations, cuts, scratches or other unusual conditions. Do not use this or any other permanent haircolouring product if you have a rash on your face or sensitive, irritated and damaged scalp. In case of a reaction while colouring your hair, such as stinging, rash or burning sensation on the skin, rinse out immediately and discontinue use.
- Do not use on hair that has been lightened, bleached, highlighted, coloured blond or has been coloured with henna.
- If your hair has been coloured with metal dyes consult manufacturer.
- Remove all metal objects and jewelry before colouring and keep them away during colouring.
- Do not mix this product with any other product.
- Keep the empty package for a few days, in case you experience a reaction.
- Contact the manufacturer and/or the relevant national authority if you have experienced an allergic reaction.
- For external use only.
- Do not use on body hair.
- Avoid prolonged skin contact.
- When possible, remove contact lenses before applying this product.
- Avoid contact with eyes. In case of contact, rinse immediately and thoroughly with cool water. If irritation persists, call a doctor.
- This product is not intended for use on persons under the age of 16.

IN RARE CASES, USE OF HAIR DYE HAS BEEN ASSOCIATED WITH SKIN DEPIGMENTATION (SKIN LIGHTENING OR LOSS OF SKIN COLOUR), WHICH MAY BE TEMPORARY OR PERMANENT. IF YOU NOTICE ANY SKIN DEPIGMENTATION, DISCONTINUE USE IMMEDIATELY.

DO NOT USE THIS PRODUCT AT ALL IF YOU HAVE SKIN DEPIGMENTATION PROBLEMS SUCH AS WHITE PATCHES ON YOUR SKIN (A CONDITION CALLED VITILIGO) OR IF YOU HAVE A FAMILY HISTORY OF SKIN DEPIGMENTATION PROBLEMS, AS AN ALLERGIC REACTION MAY CAUSE TEMPORARY OR PERMANENT LOSS OF SKIN PIGMENT.

Contains phenylenediamines.

DO NOT USE ON EYEBROWS OR EYELASHES; to do so may cause blindness.

KEEP ALL HAIRCOLOURING PRODUCTS OUT OF REACH OF CHILDREN. DO NOT INGEST. IF SWALLOWED, GET MEDICAL HELP OR CONTACT A POISON CONTROL CENTER RIGHT AWAY.

JUST FOR MEN® CONTROL GX® Grey Reducing Anti-Dandruff Shampoo

1% pyrithione zinc

IMPORTANT: READ AND FOLLOW THE 48-HOUR SKIN ALLERGY TEST INSTRUCTIONS AND SAFETY WARNINGS BEFORE YOU USE THIS PRODUCT.

USAGE DIRECTIONS

You must perform the 48-Hour Skin Allergy Test before first use and whenever you have not used this shampoo for 2 consecutive weeks or more. DO NOT USE on hair that has been lightened, bleached, highlighted, coloured blond or has been coloured with henna.

Get the look you want: Use daily until you like what you see, then regularly to maintain the look you like.

Keep it that way: Once you’ve reached the level of grey reduction you like, you can reduce the frequency of use, alternating with another anti-dandruff shampoo (preferably a gentle shampoo, so you don’t start losing your great look).

1) Peel off freshness tab under cap. Do not use if missing or broken. Do not leave tube open between uses.

2) Massage into wet hair using the palms of your hands, NOT your fingertips, to avoid nail staining. Wash hands thoroughly with soap and water. Leave on for about 1 minute before rinsing hair thoroughly.

3) Wash hands thoroughly again with soap and water, and dry hair with an old or dark towel.

4) IMPORTANT: Rinse off any product that has dripped or splattered. Failure to do so can result in staining of surfaces. Store tube facing cap down.

FREQUENTLY ASKED QUESTIONS

1) Will the product stain my skin? Some men with very dry skin may experience temporary staining of fingers and nails. This can be avoided by following these precautions:

- Moisturise hands with a hand or body moisturiser before using the product.
- Use the palms of your hands to apply, not your fingertips.
- Wash hands and nails thoroughly with soap immediately after using this product.
- Should you experience any nail staining, gently clean with toothpaste and a toothbrush.
- If you still experience skin or nail staining, use disposable gloves.

2) Does the product rub off? Control GX permanently reduces your grey and does not rub off if you rinse your hair thoroughly. To be on the safe side, use a dark or old towel to dry hair. Any stains on towels should come off by washing them as long as you don’t wait too long.

3) Will the product stain surfaces? Control GX may stain surfaces if you don’t rinse it off thoroughly. Check surfaces for any dripped or splattered product after use. Rinse off with water to avoid staining. If you see staining, use a non-abrasive cleaner with bleach. Always test in an inconspicuous area first.

4) I see some dark spots in the product. Is that normal? Control GX may develop dark spots in the tube over time. This is normal because Control GX is sensitive to oxygen. As the product is opened and closed for use, trace amounts of oxygen can enter the tube. Darkening in the tube does not affect the results of the product. Store the tube facing cap down.

5) Can I use with another haircolour? DO NOT USE Control GX on hair that has been lightened, bleached, highlighted, coloured blond or has been coloured with henna. You may use Control GX on hair that has been previously darkened, however the colour can become darker and change tone. If you have visible colour in your hair, for best results wait until it has grown out before using Control GX.

6) Can I use on facial or body hair? No, Control GX Anti-Dandruff was designed and tested only for use on head hair.

PRINCIPAL DISPLAY PANEL

REDUCES GREY WITH EACH SHAMPOO

JUST FOR MEN®

CONTROL GX® ANTI-DANDRUFF

GREY REDUCING ANTI-DANDRUFF SHAMPOO

1% pyrithione zinc

GRADUALLY REDUCES GREY

SUBTLE, NATURAL-LOOKING RESULTS

GENTLY CLEANS & CONTROLS DANDRUFF

FOR ANY SHADE OF HAIR. SEE BACK PANEL*

4 FL. OZ. (118 mL)

ANTI-DANDRUFF + HAIRCOLOUR SHAMPOO

IMPORTANT: Haircolour can cause allergic reactions. Follow Safety Warnings on side panel.